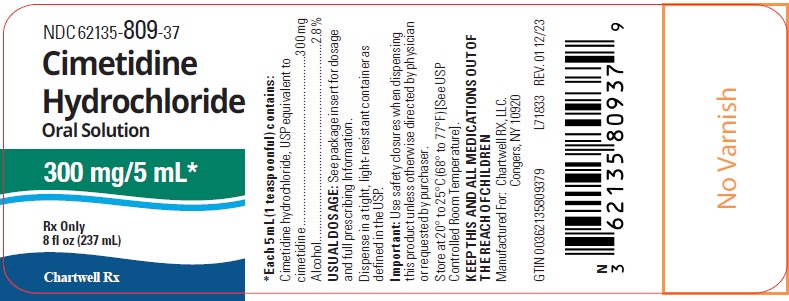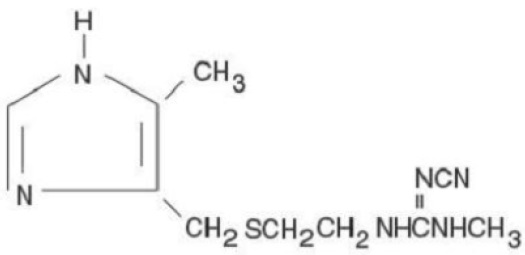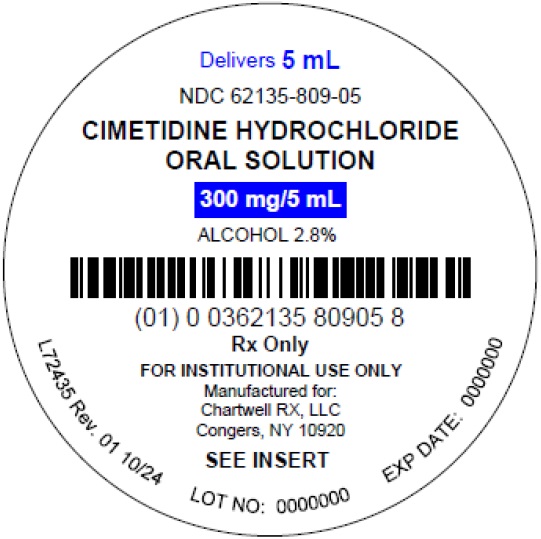 DRUG LABEL: CIMETIDINE HYDROCHLORIDE
NDC: 62135-809 | Form: SOLUTION
Manufacturer: Chartwell RX, LLC
Category: prescription | Type: HUMAN PRESCRIPTION DRUG LABEL
Date: 20260205

ACTIVE INGREDIENTS: CIMETIDINE HYDROCHLORIDE 300 mg/5 mL
INACTIVE INGREDIENTS: ALCOHOL; SODIUM PHOSPHATE, DIBASIC, HEPTAHYDRATE; FD&C RED NO. 40; FD&C YELLOW NO. 6; HYDROCHLORIC ACID; MENTHOL, UNSPECIFIED FORM; METHYLPARABEN; POLOXAMER 188; PROPYLENE GLYCOL; PROPYLPARABEN; SODIUM HYDROXIDE; SACCHARIN SODIUM; SORBITOL SOLUTION; WATER

CIMETIDINE HYDROCHLORIDE ORAL SOLUTION

DESCRIPTION

Cimetidine is a histamine H2-receptor antagonist. Chemically it is N"-cyano-N-methyl-N'-[2-[[(5-methyl-1Himidazol-4-yl)methyl]thio]-ethyl],guanidine.

The molecular formula for Cimetidine Hydrochloride, USP is C10H16N6S•HCl and the molecular weight is 288.80 the structural formula of Cimetidine Hydrochloride is:

Cimetidine contains an imidazole ring, and is chemically related to histamine.

Cimetidine has a bitter taste and characteristic odor.

Solubility Characteristics

Cimetidine Hydrochloride is freely soluble in water, soluble in alcohol, very slightly soluble in chloroform and practically insoluble in ether.

Each 5 mL (1 teaspoonful), for oral administration, contains Cimetidine Hydrochloride, equivalent to Cimetidine 300 mg; alcohol, 2.8%. In addition, the oral solution contains the following inactive ingredients: consist of dibasic sodium phosphate, heptahydrate; FD&C Red #40; FD&C Yellow #6; hydrochloric acid; menthol; methylparaben; natural orange Wonf; poloxamer 188; propylene glycol; propylparaben; Prosweet liquid; sodium hydroxide; sodium saccharin dihydrate; sorbitol solution; and purified water. The pH range is 5.1 to 5.7.

CLINICAL PHARMACOLOGY

Cimetidine competitively inhibits the action of histamine at the histamine H2receptors of the parietal cells and thus is a histamine H2receptor antagonist.

Cimetidine is not an anticholinergic agent. Studies have shown that cimetidine inhibits both daytime and nocturnal basal gastric acid secretion. Cimetidine also inhibits gastric acid secretion stimulated by food, histamine, pentagastrin, caffeine and insulin.

Antisecretory Activity

1. Acid Secretion: Nocturnal: Cimetidine 800 mg orally at bedtime reduces mean hourly H+ activity by greater than 85% over an eight-hour period in duodenal ulcer patients, with no effect on daytime acid secretion. Cimetidine 1600 mg orally h.s. produces 100% inhibition of mean hourly H+ activity over an eight-hour period in duodenal ulcer patients, but also reduces H+ activity by 35% for an additional five hours into the following morning. Cimetidine 400 mg b.i.d. and 300 mg q.i.d. decrease nocturnal acid secretion in a dose-related manner, i.e., 47% to 83% over a six-to eight-hour period and 54% over a nine-hour period, respectively.
  Food Stimulated: During the first hour after a standard experimental meal, oral cimetidine 300 mg inhibited gastric acid secretion in duodenal ulcer patients by at least 50%. During the subsequent two hours cimetidine inhibited gastric acid secretion by at least 75%.
  The effect of a 300 mg breakfast dose of cimetidine continued for at least four hours and there was partial suppression of the rise in gastric acid secretion following the luncheon meal in duodenal ulcer patients. This suppression of gastric acid output was enhanced and could be maintained by another 300 mg dose of cimetidine given with lunch.
  In another study, cimetidine 300 mg was given with the meal increased gastric pH as compared with placebo.
  Mean Gastric pH
   | Cimetidine | Placebo
  1 hour | 3.5 | 2.6
  2 hours | 3.1 | 1.6
  3 hours | 3.8 | 1.9
  4 hours | 6.1 | 2.2
  24-Hour Mean H+ Activity: Cimetidine 800 mg h.s., 400 mg b.i.d. and 300 mg q.i.d. all provide a similar, moderate (less than 60%) level of 24-hour acid suppression. However, the 800 mg h.s. regimen exerts its entire effect on nocturnal acid, and does not affect daytime gastric physiology.
  Chemically Stimulated: Oral cimetidine significantly inhibited gastric acid secretion stimulated by betazole (an isomer of histamine), pentagastrin, caffeine and insulin as follows:
  Stimulant | Stimulant Dose | Cimetidine | % Inhibition
  Betazole | 1.5 mg/kg (sc) | 300 mg (po) | 85% at 21/2 hours
  Pentagastrin | 6 mcg/kg/hr (iv) | 100 mg/hr (iv) | 60% at 1 hour
  Caffeine | 5 mg/kg/hr (iv) | 300 mg (po) | 100% at 1 hour
  Insulin | 0.03 units/kg/hr (iv) | 100 mg/hr (iv) | 82% at 1 hour
  When food and betazole were used to stimulate secretion, inhibition of hydrogen ion concentration usually ranged from 45 to 75% and the inhibition of volume ranged from 30 to 65%.
2. Pepsin: Oral cimetidine 300 mg reduced total pepsin output as a result of the decrease in volume of gastric juice.
3. Intrinsic Factor: Intrinsic factor secretion was studied with betazole as a stimulant. Oral cimetidine 300 mg inhibited the rise in intrinsic factor concentration produced by betazole, but some intrinsic factor was secreted at all times.

Other

Lower Esophageal Sphincter Pressure and Gastric Emptying

Cimetidine has no effect on lower esophageal sphincter (LES) pressure or the rate of gastric emptying.

Pharmacokinetics

Cimetidine is rapidly absorbed after oral administration and peak levels occur in 45 to 90 minutes. The half-life of cimetidine is approximately 2 hours. Both oral and parenteral (I.V. or I.M.) administration provide comparable periods of therapeutically effective blood levels; blood concentrations remain above that required to provide 80% inhibition of basal gastric acid secretion for 4 to 5 hours following a dose of 300 mg.

The principal route of excretion of cimetidine is the urine. Following parenteral administration, most of the drug is excreted as the parent compound; following oral administration, the drug is more extensively metabolized, the sulfoxide being the major metabolite. Following a single oral dose, 48% of the drug is recovered from the urine after 24 hours as the parent compound. Following I.V. or I.M. administration, approximately 75% of the drug is recovered from the urine after 24 hours as the parent compound.

Clinical Trials

Duodenal Ulcer

Cimetidine has been shown to be effective in the treatment of active duodenal ulcer and, at reduced dosage, in maintenance therapy following healing of active ulcers.

Active Duodenal Ulcer: Cimetidine accelerates the rate of duodenal ulcer healing. Healing rates reported in U.S. and foreign controlled trials with oral cimetidine are summarized below, beginning with the regimen providing the lowest nocturnal dose.

Duodenal Ulcer Healing Rates with Various Oral Cimetidine Dosage Regimens*

REGIMEN | 300 MG q.i.d. | 400 MG b.i.d. | 800 MG h.s. | 1600 MG h.s.
Week 4 | 68% | 73% | 80% | 86%
Week 6 | 80% | 80% | 89% | --
Week 8 | -- | 92% | 94% | --

*Averages from controlled clinical trials.

A U.S., double-blind, placebo-controlled, dose-ranging study demonstrated that all once-daily at bedtime (h.s.) cimetidine regimens were superior to placebo in ulcer healing and that cimetidine 800 mg h.s. healed 75% of patients at four weeks. The healing rate with 800 mg h.s. was significantly superior to 400 mg h.s. (66%) and not significantly different from 1600 mg h.s. (81%).

In the U.S. dose-ranging trial, over 80% of patients receiving cimetidine 800 mg h.s. experienced nocturnal pain relief after one day. Relief from daytime pain was reported in approximately 70% of patients after two days. As with ulcer healing, the 800 mg h.s. dose was superior to 400 mg h.s. and not different from 1600 mg h.s.

In foreign, double-blind studies with cimetidine 800 mg h.s. 79 to 85% of patients were healed at four weeks. While short-term treatment with cimetidine can result in complete healing of the duodenal ulcer, acute therapy will not prevent ulcer recurrence after cimetidine has been discontinued. Some follow-up studies have reported that the rate of recurrence once therapy was discontinued was slightly higher for patients healed on cimetidine than for patients healed on other forms of therapy; however, the cimetidine-treated patients generally had more severe disease.

Maintenance Therapy in Duodenal Ulcer: Treatment with a reduced dose of cimetidine has been proven effective as maintenance therapy following healing of active duodenal ulcers.

In numerous placebo-controlled studies conducted worldwide, the percent of patients with observed ulcers at the end of 1 year's therapy with cimetidine 400 mg h.s. was significantly lower (10% to 45%) than in patients receiving placebo (44% to 70%). Thus, from 55% to 90% of patients were maintained free of observed ulcers at the end of 1 year with cimetidine 400 mg h.s.

Factors such as smoking, duration and severity of disease, gender, and genetic traits may contribute to variations in actual percentages.

Trials of other anti-ulcer therapy, whether placebo-controlled, positive-controlled or open, have demonstrated a range of results similar to that seen with cimetidine.

Active Benign Gastric Ulcer

Cimetidine has been shown to be effective in the short-term treatment of active benign gastric ulcer. In a multicenter, double-blind U.S. study, patients with endoscopically confirmed benign gastric ulcer were treated with cimetidine 300 mg four times a day or with placebo for 6 weeks. Patients were limited to those with ulcers ranging from 0.5 to 2.5 cm in size. Endoscopically confirmed healing at 6 weeks was seen in significantly* more cimetidine-treated patients than in patients receiving placebo, as shown:

 | Cimetidine | Placebo
week 2 | 14/63 (22%) | 7/63 (11%)
total at week 6 | 43/65 (66%)* | 30/67 (45%)

*p<0.05

In a similar multicenter U.S. study of the 800 mg h.s. oral regimen, the endoscopically confirmed healing rates were:

 | Cimetidine | Placebo
total at week 6 | 63/83 (76%)* | 44/80 (55%)

*p = 0.005

Similarly, in worldwide double-blind clinical studies, endoscopically evaluated benign gastric ulcer healing rates were consistently higher with cimetidine than with placebo.

Gastroesophageal Reflux Disease

In two multicenter, double-blind, placebo-controlled studies in patients with gastroesophageal reflux disease (GERD) and endoscopically proven erosions and/or ulcers, cimetidine was significantly more effective than placebo in healing lesions. The endoscopically confirmed healing rates were:

Trial |  | Cimetidine; (800 mg b.i.d.) | Cimetidine; (400 mg q.i.d.) | Placebo | p-Value; (800 mg b.i.d. vs. placebo)
1 | Week 6 | 45% | 52% | 26% | 0.02
1 | Week 12 | 60% | 66% | 42% | 0.02
2 | Week 6 | 50% |  | 20% | <0.01
2 | Week 12 | 67% |  | 36% | <0.01

In these trials cimetidine was superior to placebo by most measures in improving symptoms of day- and night-time heartburn, with many of the differences statistically significant. The q.i.d. regimen was generally somewhat better than the b.i.d. regimen where these were compared.

Pathological Hypersecretory Conditions (such as Zollinger-Ellison Syndrome)

Cimetidine significantly inhibited gastric acid secretion and reduced occurrence of diarrhea, anorexia and pain in patients with pathological hypersecretion associated with Zollinger-Ellison Syndrome, systemic mastocytosis and multiple endocrine adenomas. Use of cimetidine was also followed by healing of intractable ulcers.

INDICATIONS AND USAGE

Cimetidine Hydrochloride Oral Solution is indicated in:

(1) Short-term treatment of active duodenal ulcer. Most patients heal within 4 weeks and there is rarely reason to use cimetidine at full dosage for longer than 6 to 8 weeks (see Dosage and Administration-Duodenal Ulcer). Concomitant antacids should be given as needed for relief of pain. However, simultaneous administration of oral cimetidine and antacids is not recommended, since antacids have been reported to interfere with the absorption of oral cimetidine.

(2) Maintenance therapy for duodenal ulcer patients at reduced dosage after healing of active ulcer. Patients have been maintained on continued treatment with cimetidine 400 mg h.s. for periods of up to 5 years.

(3) Short-term treatment of active benign gastric ulcer. There is no information concerning usefulness of treatment periods of longer than 8 weeks.

(4) Erosive gastroesophageal reflux disease (GERD). Erosive esophagitis diagnosed by endoscopy. Treatment is indicated for 12 weeks for healing of lesions and control of symptoms. The use of cimetidine beyond 12 weeks has not been established (see Dosage and Administration-GERD).

(5) The treatment of pathological hypersecretory conditions (i.e., Zollinger-Ellison Syndrome, systemic mastocytosis, multiple endocrine adenomas).

CONTRAINDICATIONS

Cimetidine is contraindicated for patients known to have hypersensitivity to the product.

PRECAUTIONS

General

Symptomatic response to cimetidine therapy does not preclude the presence of a gastric malignancy. There have been rare reports of transient healing of gastric ulcers despite subsequently documented malignancy. Reversible confusional states (see Adverse Reactions) have been observed on occasion, predominantly, but not exclusively, in severely ill patients. Advancing age (50 or more years) and preexisting liver and/or renal disease appear to be contributing factors. In some patients these confusional states have been mild and have not required discontinuation of cimetidine therapy. In cases where discontinuation was judged necessary, the condition usually cleared within 3 to 4 days of drug withdrawal.

Drug Interactions

Cimetidine, apparently through an effect on certain microsomal enzyme systems, has been reported to reduce the hepatic metabolism of warfarin-type anticoagulants, phenytoin, propranolol, nifedipine, chlordiazepoxide, diazepam, certain tricyclic antidepressants, lidocaine, theophylline and metronidazole, thereby delaying elimination and increasing blood levels of these drugs.

Clinically significant effects have been reported with the warfarin anticoagulants; therefore, close monitoring of prothrombin time is recommended, and adjustment of the anticoagulant dose may be necessary when cimetidine is administered concomitantly. Interaction with phenytoin, lidocaine and theophylline has also been reported to produce adverse clinical effects.

However, a crossover study in healthy subjects receiving either cimetidine 300 mg q.i.d. or 800 mg h.s. concomitantly with a 300 mg b.i.d. dosage of theophylline extended-release tablets demonstrated less alteration in steady-state theophylline peak serum levels with the 800 mg h.s. regimen, particularly in subjects aged 54 years and older. Data beyond ten days are not available (Note: All patients receiving theophylline should be monitored appropriately, regardless of concomitant drug therapy.)

Dosage of the drugs mentioned above and other similarly metabolized drugs, particularly those of low therapeutic ratio or in patients with renal and/or hepatic impairment, may require adjustment when starting or stopping concomitantly administered cimetidine to maintain optimum therapeutic blood levels.

Alteration of pH may affect absorption of certain drugs (e.g., ketoconazole). If these products are needed, they should be given at least 2 hours before cimetidine administration.

Additional clinical experience may reveal other drugs affected by the concomitant administration of cimetidine.

Carcinogenesis, Mutagenesis, Impairment of Fertility

In a 24-month toxicity study conducted in rats, at dose levels of 150, 378 and 950 mg/kg/day (approximately 8 to 48 times the recommended human dose), there was a small increase in the incidence of benign Leydig cell tumors in each dose group; when the combined drug-treated groups and control groups were compared, this increase reached statistical significance. In a subsequent 24-month study, there were no differences between the rats receiving 150 mg/kg/day and the untreated controls. However, a statistically significant increase in benign Leydig cell tumor incidence was seen in rats that received 378 and 950 mg/kg/day. These tumors were common in control groups as well as treated groups and the difference became apparent only in aged rats.

Cimetidine has demonstrated a weak antiandrogenic effect. In animal studies this was manifested as reduced prostate and seminal vesicle weights. However, there was no impairment of mating performance or fertility, nor any harm to the fetus in these animals at doses 8 to 48 times the full therapeutic dose of cimetidine as compared with controls. The cases of gynecomastia seen in patients treated for one month or longer may be related to this effect.

In human studies, cimetidine has been shown to have no effect on spermatogenesis, sperm count, motility, morphology or in vitrofertilizing capacity.

Pregnancy

Teratogenic Effects.

Reproduction studies have been performed in rats, rabbits and mice at doses up to 40 times the normal human dose and have revealed no evidence of impaired fertility or harm to the fetus due to cimetidine. There are, however, no adequate and well-controlled studies in pregnant women. Because animal reproductive studies are not always predictive of human response, this drug should be used during pregnancy only if clearly needed.

Nursing Mothers

Cimetidine is secreted in human milk and, as a general rule, nursing should not be undertaken while a patient is on a drug.

Pediatric Use

Clinical experience in pediatric patients is limited. Therefore, cimetidine therapy cannot be recommended for pediatric patients under 16, unless, in the judgement of the physician, anticipated benefits outweigh the potential risks. In very limited experience, doses of 20 to 40 mg/kg per day have been used.

Immunocompromised Patients

In immunocompromised patients, decreased gastric acidity, including that produced by acid-suppressing agents such as cimetidine, may increase the possibility of a hyperinfection of strongyloidiasis.

ADVERSE REACTIONS

To report SUSPECTED ADVERSE REACTIONS, contact Chartwell RX, LLC. at 1-845-232-1683 or FDA at 1-800-FDA-1088 or www.fda.gov/medwatch.

Adverse effects reported in patients taking cimetidine are described below by body system.

Incidence figures of 1 in 100 and greater are generally derived from controlled clinical studies.

Gastrointestinal

Diarrhea (usually mild) has been reported in approximately 1 in 100 patients.

CNS

Headaches ranging from mild to severe have been reported in 3.5% of 924 patients taking 1600 mg/day, 2.1% of 2,225 patients taking 800 mg/day and 2.3% of 1,897 patients taking placebo. Dizziness and somnolence (usually mild) have been reported in approximately 1 in 100 patients on either 1600 mg/day or 800 mg/day.

Reversible confusional states, e.g., mental confusion, agitation, psychosis, depression, anxiety, hallucinations, disorientation, have been reported predominantly, but not exclusively, in severely ill patients. They have usually developed within 2 to 3 days of initiation of cimetidine therapy and have cleared within 3 to 4 days of discontinuation of the drug.

Endocrine

Gynecomastia has been reported in patients treated for one month or longer. In patients being treated for pathological hypersecretory states, this occurred in about 4% of cases while in all others the incidence was 0.3% to 1% in various studies. No evidence of induced endocrine dysfunction was found, and the condition remained unchanged or returned toward normal with continuing cimetidine treatment.

Reversible impotence has been reported in patients with pathological hypersecretory disorders, e.g., Zollinger-Ellison Syndrome, receiving cimetidine, particularly in high doses, for at least 12 months (range 12 to 79 months, mean 38 months). However, in large-scale surveillance studies at regular dosage, the incidence has not exceeded that commonly reported in the general population.

Hematologic

Decreased white blood cell counts in cimetidine-treated patients (approximately 1 per 100,000 patients), including agranulocytosis (approximately 3 per million patients), have been reported, including a few reports of recurrence on rechallenge. Most of these reports were in patients who had serious concomitant illnesses and received drugs and/or treatment known to produce neutropenia. Thrombocytopenia (approximately 3 per million patients) and, very rarely, cases of pancytopenia or aplastic anemia have also been reported. As with some other H2-receptor antagonists, there have been extremely rare reports of immune hemolytic anemia.

Hepatobiliary

Dose-related increases in serum transaminase have been reported. In most cases they did not progress with continued therapy and returned to normal at the end of the therapy. There have been rare reports of cholestatic or mixed cholestatic-hepatocellular effects. These were usually reversible. Because of the predominance of cholestatic features, severe parenchymal injury is considered highly unlikely. However, as in occasional liver injury with other H2-receptor antagonists, in exceedingly rare circumstances fatal outcomes have been reported. There has been reported a single case of biopsy-proven periportal hepatic fibrosis in a patient receiving cimetidine.

Rare cases of pancreatitis, which cleared on withdrawal of the drug, have been reported.

Hypersensitivity

Rare cases of fever and allergic reactions including anaphylaxis and hypersensitivity vasculitis, which cleared on withdrawal of the drug, have been reported.

Renal

Small, possibly dose-related increases in plasma creatinine, presumably due to competition for renal tubular secretion, are not uncommon and do not signify deteriorating renal function. Rare cases of interstitial nephritis and urinary retention, which cleared on withdrawal of the drug, have been reported.

Cardiovascular

Rare cases of bradycardia, tachycardia and A-V heart block have been reported with H2-receptor antagonists.

Musculoskeletal

There have been rare reports of reversible arthralgia and myalgia; exacerbation of joint symptoms in patients with preexisting arthritis has also been reported. Such symptoms have usually been alleviated by a reduction in cimetidine dosage. Rare cases of polymyositis have been reported but no causal relationship has been established.

Integumental

Mild rash and, very rarely, cases of severe generalized skin reactions including Stevens-Johnson syndrome, epidermal necrolysis, erythema multiforme, exfoliative dermatitis and generalized exfoliative erythroderma have been reported with H2-receptor antagonists.

Reversible alopecia has been reported very rarely.

Immune Function:

There have been extremely rare reports of strongyloidiasis hyperinfection in immunocompromised patients.

OVERDOSAGE

Studies in animals indicate that toxic doses are associated with respiratory failure and tachycardia that may be controlled by assisted respiration and the administration of a beta-blocker.

Reported acute ingestions orally of up to 20 grams have been associated with transient adverse effects similar to those encountered in normal clinical experience. The usual measures to remove unabsorbed material from the gastrointestinal tract, clinical monitoring, and supportive therapy should be employed.

There have been reports of severe CNS symptoms, including unresponsiveness, following ingestion of between 20 and 40 grams of cimetidine, and extremely rare reports following concomitant use of multiple CNS-active medications and ingestion of cimetidine at doses less than 20 grams. An elderly, terminally ill dehydrated patient with organic brain syndrome receiving concomitant antipsychotic agents and cimetidine 4800 mg intravenously over a 24-hour period experienced mental deterioration with reversal on Cimetidine discontinuation.

There have been two deaths in adults who have been reported to ingest over 40 grams orally on a single occasion.

DOSAGE AND ADMINISTRATION

Duodenal Ulcer

Active Duodenal Ulcer: Clinical studies have indicated that suppression of nocturnal acid is the most important factor in duodenal ulcer healing (see Clinical Pharmacology-Antisecretory Activity-Acid Secretion). This is supported by recent clinical trials (see Clinical Pharmacology-Clinical Trials Duodenal Ulcer-Active Duodenal Ulcer). Therefore, there is no apparent rationale, except for familiarity with use, for treating with anything other than a once-daily at bedtime dosage regimen (h.s.).

In a U.S. oral dose-ranging study of 400 mg h.s., 800 mg h.s. and 1600 mg h.s., a continuous dose response relationship for ulcer healing was demonstrated.

However, 800 mg h.s. is the dose of choice for most patients, as it provides a high healing rate (the difference between 800 mg h.s. and 1600 mg h.s. being small), maximal pain relief, a decreased potential for drug interactions (see Precautions-Drug Interactions) and maximal patient convenience. Patients unhealed at 4 weeks, or those with persistent symptoms, have been shown to benefit from two to four weeks of continued therapy.

It has been shown that patients who both have an endoscopically demonstrated ulcer larger than 1 cm and are also heavy smokers (i.e., smoke one pack of cigarettes or more per day) are more difficult to heal. There is some evidence which suggests that more rapid healing can be achieved in this subpopulation with cimetidine 1,600 mg at bedtime. While early pain relief with either 800 mg h.s. or 1,600 mg h.s. is equivalent in all patients, 1,600 mg h.s. provides an appropriate alternative when it is important to ensure healing within four weeks for this subpopulation. Alternatively, approximately 94% of all patients will also heal in eight weeks with cimetidine 800 mg h.s.

Other cimetidine regimens in the U.S. which have been shown to be effective are: 300 mg four times daily, with meals and at bedtime, the original regimen with which U.S. physicians have the most experience, and 400 mg twice daily, in the morning and at bedtime (see Clinical Pharmacology Clinical Trials-Duodenal Ulcer-Duodenal Ulcer).

Concomitant antacids should be given as needed for relief of pain. However, simultaneous administration of cimetidine and antacids is not recommended, since antacids have been reported to interfere with the absorption of cimetidine.

While healing with cimetidine often occurs during the first week or two, treatment should be continued for 4 to 6 weeks unless healing has been demonstrated by endoscopic examination.

Maintenance Therapy for Duodenal Ulcer: In those patients requiring maintenance therapy, the recommended adult oral dose is 400 mg at bedtime.

Active Benign Gastric Ulcer

The recommended adult oral dosage for short-term treatment of active benign gastric ulcer is 800 mg h.s., or 300 mg four times a day with meals and at bedtime. Controlled clinical studies were limited to six weeks of treatment (see Clinical Pharmacology-Clinical Trials). 800 mg h.s. is the preferred regimen for most patients based upon convenience and reduced potential for drug interactions. Symptomatic response to cimetidine does not preclude the presence of a gastric malignancy. It is important to follow gastric ulcer patients to assure rapid progress to complete healing.

Erosive Gastroesophageal Reflux Disease (GERD)

The recommended adult oral dosage for the treatment of erosive esophagitis that has been diagnosed by endoscopy is 1,600 mg daily in divided doses (800 mg b.i.d. or 400 mg q.i.d.) for 12 weeks. The use of cimetidine beyond 12 weeks has not been established.

Pathological Hypersecretory Conditions (such as Zollinger-Ellison Syndrome)

Recommended adult oral dosage: 300 mg four times a day with meals and at bedtime. In some patients it may be necessary to administer higher doses more frequently. Doses should be adjusted to individual patient needs, but should not usually exceed 2400 mg per day and should continue as long as clinically indicated.

Dosage Adjustments for Patients with Impaired Renal Function

Patients with severely impaired renal function have been treated with cimetidine. However, such dosage has been very limited. On the basis of this experience the recommended dosage is 300 mg every 12 hours orally or by intravenous injection. Should the patient's condition require, the frequency of dosing may be increased to every 8 hours or even further with caution. In severe renal failure, accumulation may occur and the lowest frequency of dosing compatible with an adequate patient response should be used. When liver impairment is also present, further reductions in dosage may be necessary.

Hemodialysis reduces this level of circulating cimetidine. Ideally, the dosage schedule should be adjusted so that the timing of a scheduled dose coincides with the end of hemodialysis.

HOW SUPPLIED

Cimetidine Hydrochloride Oral Solution is available as a clear yellow, orange-flavored solution as follows:

300 mg/5 mL 8 fl oz (237 mL) bottle NDC 62135-809-37

5 mL Unit Dose Cups NDC 62135-809-05

20 Unit Dose Cups of 5 mL each NDC 62135-809-24

Store at 20° to 25°C (68° to 77°F) [See USP Controlled Room Temperature].

Dispense in a tight, light-resistant container.

Rx Only

Manufactured for
Chartwell RX, LLC.
Congers, NY 10920

Rev. 01/2026

L71834

PRINCIPAL DISPLAY PANEL

Cimetidine Hydrochloride Oral Solution 300 mg/5 mL - NDC 62135-809-37 - 8 fl oz (237 mL) Bottle Label

Cimetidine Hydrochloride Oral Solution 300 mg/5 mL - NDC 62135-809-05 - 5mL Unit dose Label